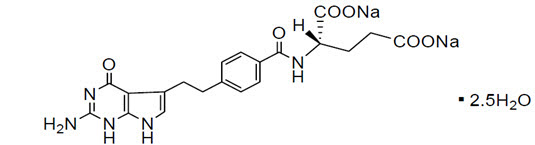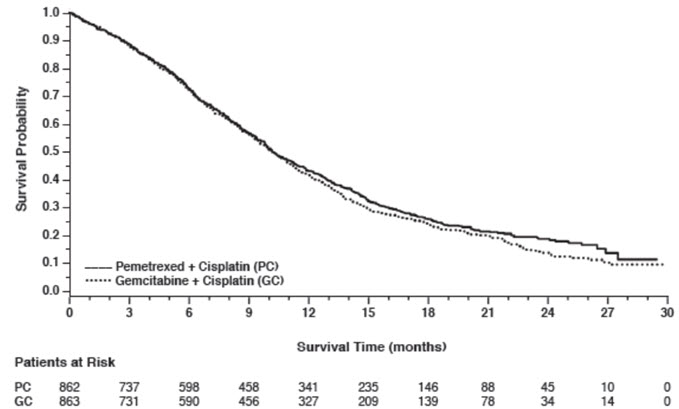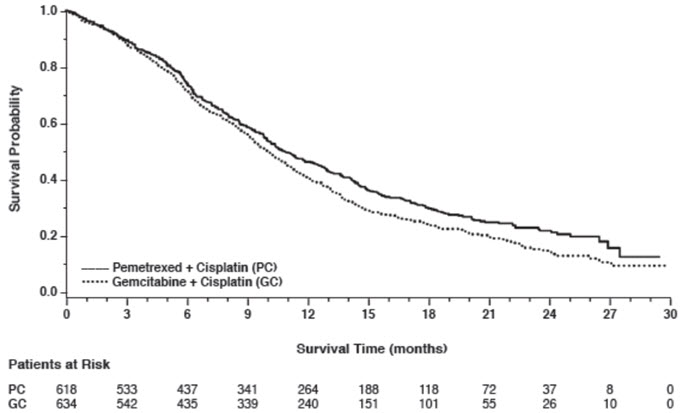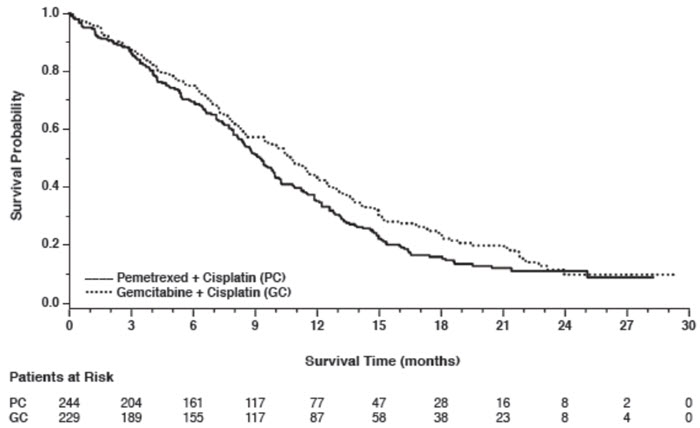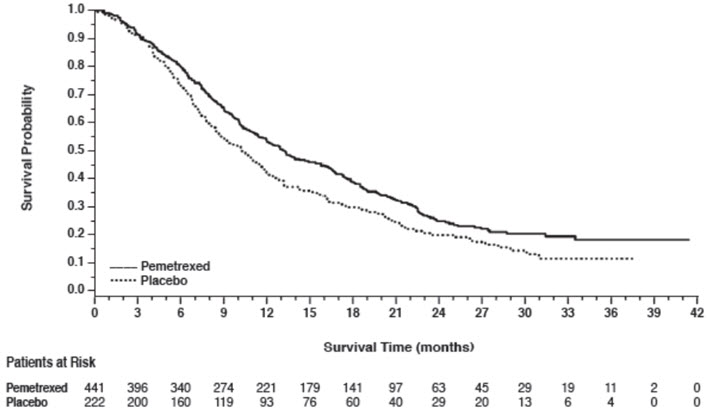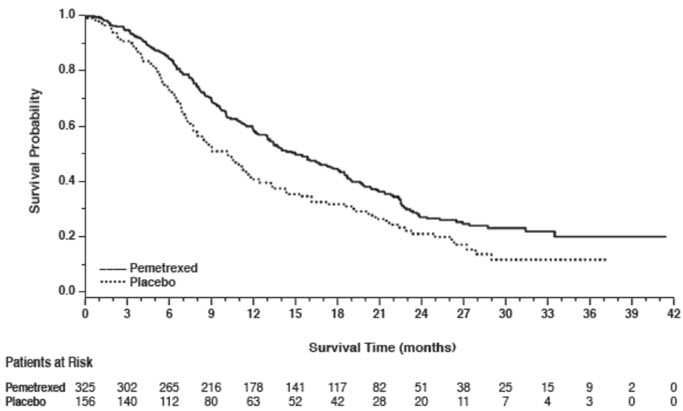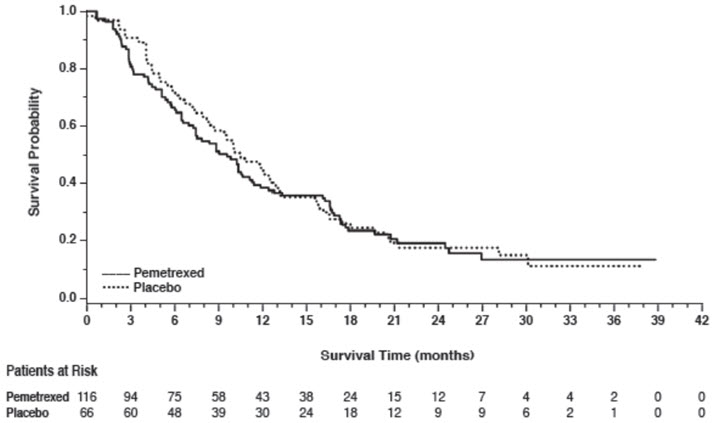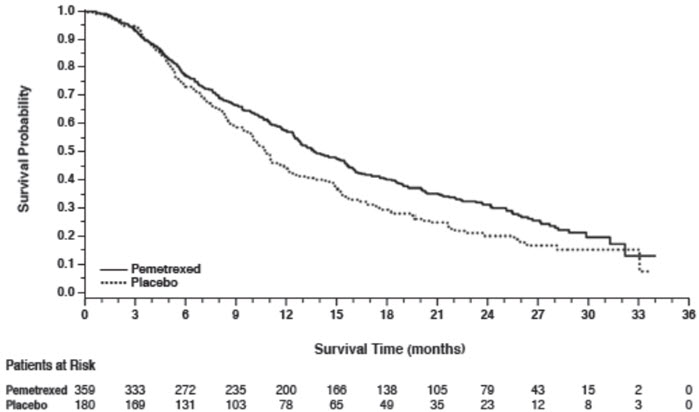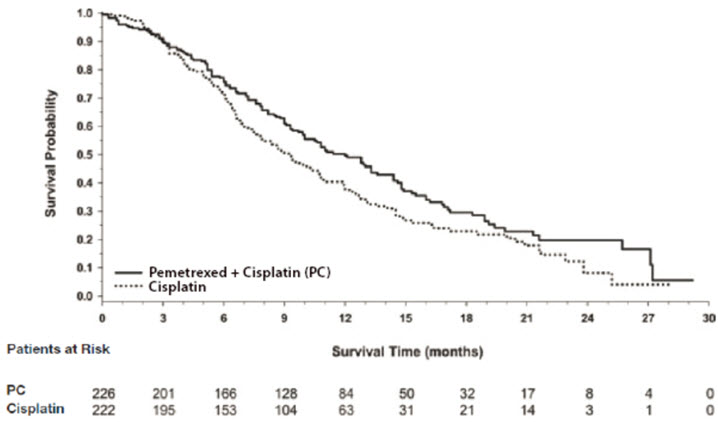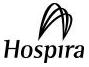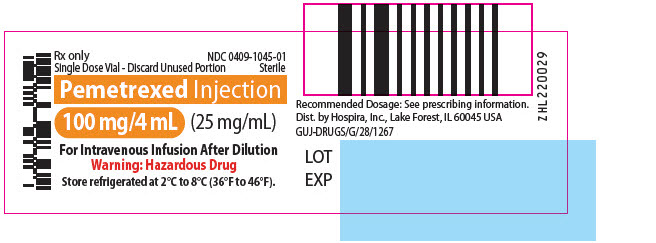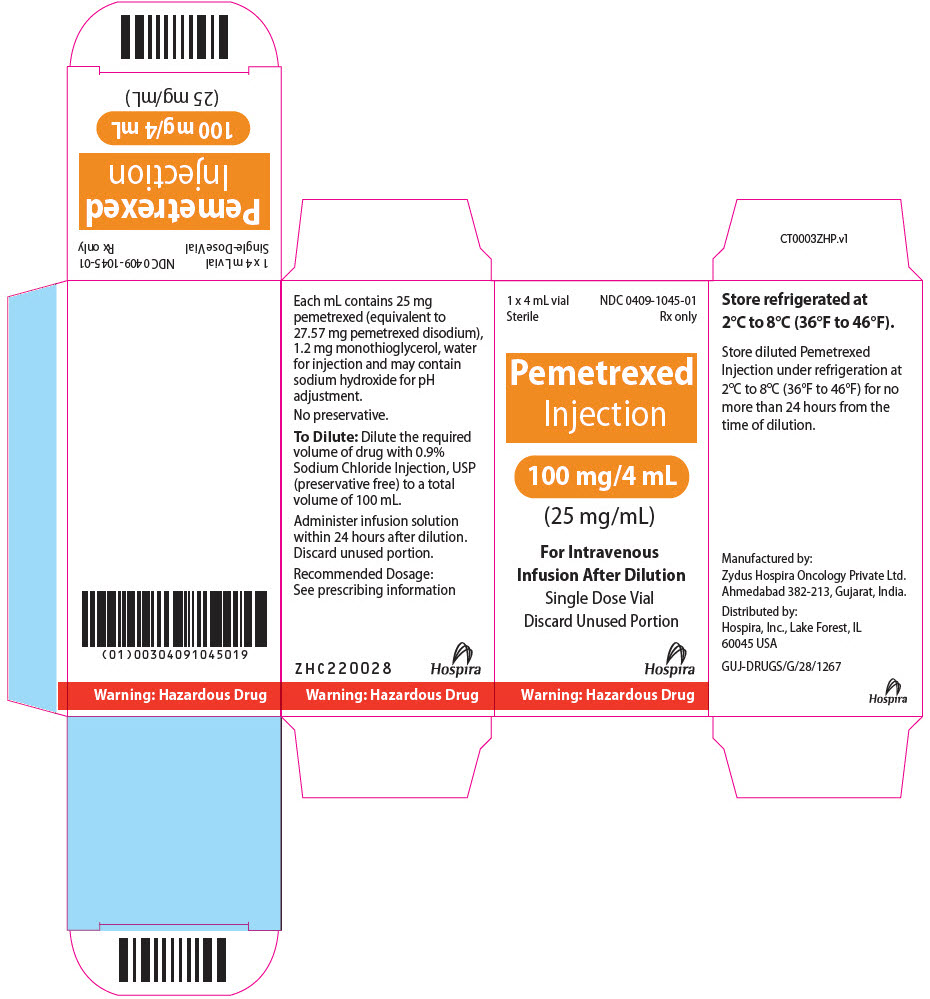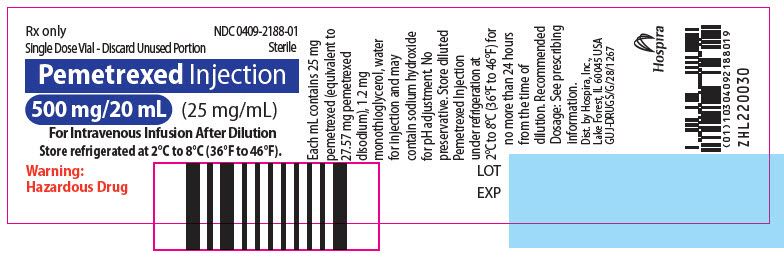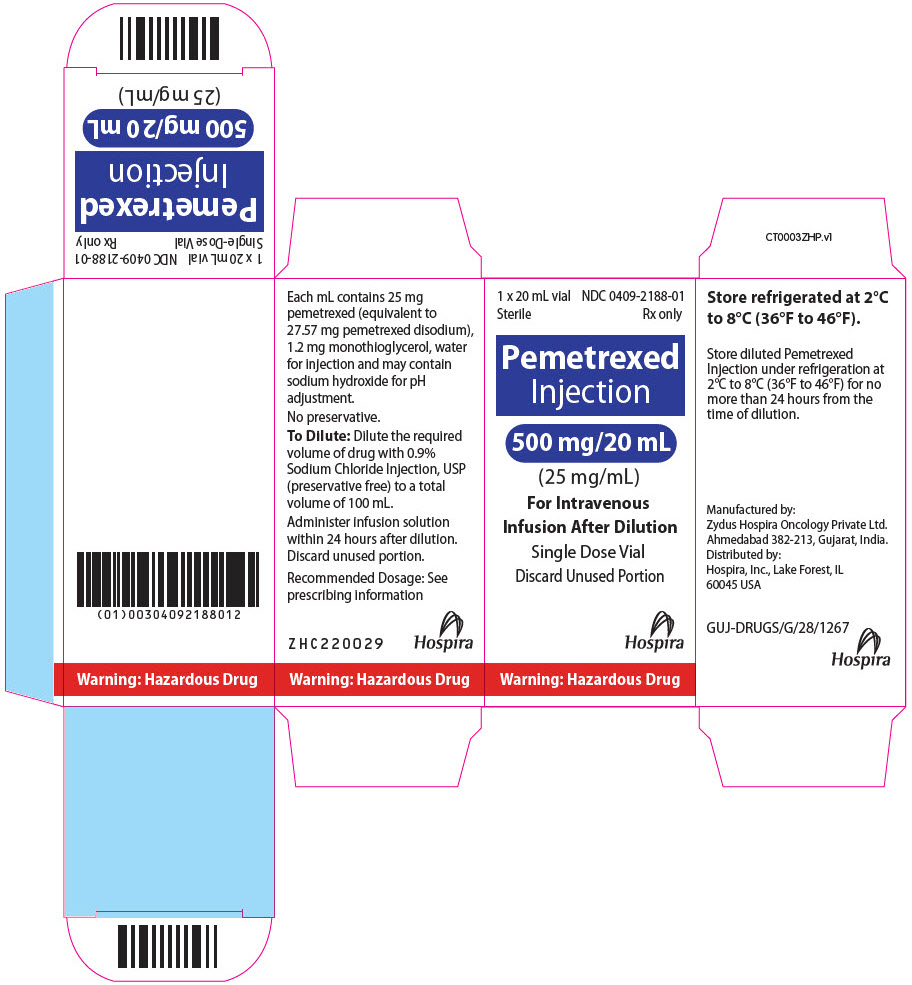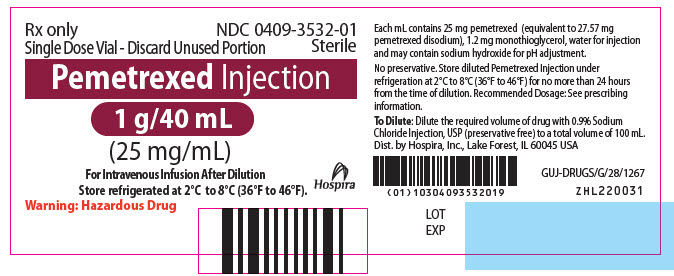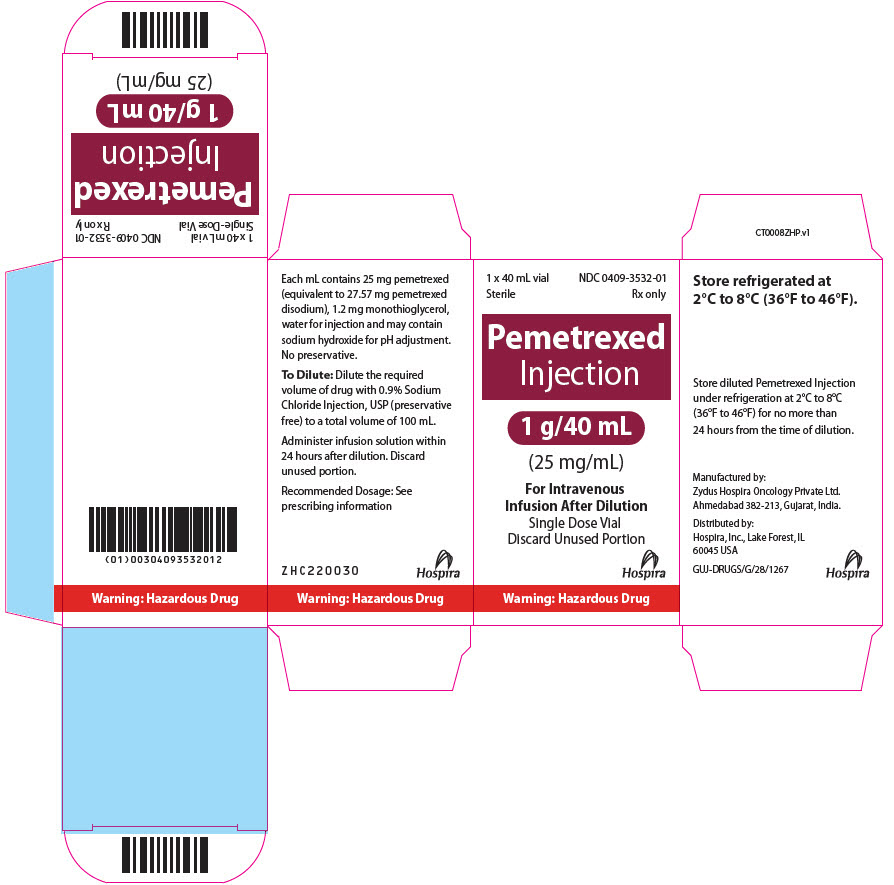 DRUG LABEL: PEMETREXED
NDC: 0409-1045 | Form: INJECTION, SOLUTION, CONCENTRATE
Manufacturer: Hospira, Inc.
Category: prescription | Type: HUMAN PRESCRIPTION DRUG LABEL
Date: 20251008

ACTIVE INGREDIENTS: PEMETREXED DISODIUM 100 mg/4 mL
INACTIVE INGREDIENTS: MONOTHIOGLYCEROL; WATER; SODIUM HYDROXIDE

HIGHLIGHTS OF PRESCRIBING INFORMATION

These highlights do not include all the information needed to use PEMETREXED INJECTION safely and effectively. See full prescribing information for PEMETREXED INJECTION.
PEMETREXED INJECTION, for intravenous use
Initial U.S. Approval: 2004

1 INDICATIONS AND USAGE

Pemetrexed Injection is a folate analog metabolic inhibitor indicated:

- In combination with cisplatin for the initial treatment of patients with locally advanced or metastatic, non-squamous, non-small cell lung cancer (NSCLC). (1.1)
- As a single agent for the maintenance treatment of patients with locally advanced or metastatic, non -squamous NSCLC whose disease has not progressed after four cycles of platinum-based first-line chemotherapy. (1.1)
- As a single agent for the treatment of patients with recurrent, metastatic non-squamous, NSCLC after prior chemotherapy. (1.1)
- Limitations of Use: Pemetrexed Injection is not indicated for the treatment of patients with squamous cell, non-small cell lung cancer. (1.1)
- Initial treatment, in combination with cisplatin, of patients with malignant pleural mesothelioma whose disease is unresectable or who are otherwise not candidates for curative surgery. (1.2)

2 DOSAGE AND ADMINISTRATION

- The recommended dose of Pemetrexed Injection, administered as a single agent or with cisplatin, in patients with creatinine clearance of 45 mL/minute or greater is 500 mg/m^2 as an intravenous infusion over 10 minutes on Day 1 of each 21-day cycle. (2.1, 2.2)
- Initiate folic acid 400 mcg to 1000 mcg orally, once daily, beginning 7 days prior to the first dose of Pemetrexed Injection and continue until 21 days after the last dose of Pemetrexed Injection. (2.4)
- Administer vitamin B12, 1 mg intramuscularly, 1 week prior to the first dose of Pemetrexed Injection and every 3 cycles. (2.4)
- Administer dexamethasone 4 mg orally, twice daily the day before, the day of, and the day after Pemetrexed Injection administration. (2.4)

3 DOSAGE FORMS AND STRENGTHS

Injection: 100 mg/4 mL (25 mg/mL) in a single-dose vial (3)
Injection: 500 mg/20 mL (25 mg/mL) in a single-dose vial (3)
Injection: 1 g/40 mL (25 mg/mL) in a single-dose vial. (3)

4 CONTRAINDICATIONS

History of severe hypersensitivity reaction to pemetrexed. (4)

5 WARNINGS AND PRECAUTIONS

- Myelosuppression: Can cause severe bone marrow suppression resulting in cytopenia and an increased risk of infection. Do not administer Pemetrexed Injection when the absolute neutrophil count is less than 1500 cells/mm^3 and platelets are less than 100,000 cells/mm^3. Initiate supplementation with oral folic acid and intramuscular vitamin B12 to reduce the severity of hematologic and gastrointestinal toxicity of Pemetrexed Injection. (2.4, 5.1)
- Renal Failure: Can cause severe, and sometimes fatal, renal failure. Do not administer when creatinine clearance is less than 45 mL/min. (2.3, 5.2)
- Bullous and Exfoliative Skin Toxicity: Permanently discontinue for severe and life-threatening bullous, blistering or exfoliating skin toxicity. (5.3)
- Interstitial Pneumonitis: Withhold for acute onset of new or progressive unexplained pulmonary symptoms. Permanently discontinue if pneumonitis is confirmed. (5.4)
- Radiation Recall: Can occur in patients who received radiation weeks to years previously; permanently discontinue for signs of radiation recall. (5.5)
- Embryo-Fetal Toxicity: Can cause fetal harm. Advise patients of the potential risk to a fetus and to use effective contraception. (5.7, 8.1, 8.3)

6 ADVERSE REACTIONS

- The most common adverse reactions (incidence ≥20%) of pemetrexed when administered as a single agent are fatigue, nausea, and anorexia. (6.1)
- The most common adverse reactions (incidence ≥20%) of pemetrexed when administered with cisplatin are vomiting, neutropenia, anemia, stomatitis/pharyngitis, thrombocytopenia, and constipation. (6.1)

To report SUSPECTED ADVERSE REACTIONS, contact Pfizer Inc., at 1-800-438-1985 or FDA at 1-800-FDA-1088 or www.fda.gov/medwatch.

7 DRUG INTERACTIONS

Ibuprofen increased risk of Pemetrexed Injection toxicity in patients with mild to moderate renal impairment. Modify the ibuprofen dosage as recommended for patients with a creatinine clearance between 45 mL/min and 79 mL/min. (2.5, 5.6, 7)

8 USE IN SPECIFIC POPULATIONS

Lactation: Advise not to breastfeed. (8.2)

FULL PRESCRIBING INFORMATION

1 INDICATIONS AND USAGE

1.1 Non-Squamous Non-Small Cell Lung Cancer (NSCLC)

Pemetrexed Injection is indicated:

- In combination with cisplatin for the initial treatment of patients with locally advanced or metastatic, non-squamous, non-small cell lung cancer (NSCLC).
- As a single agent for the maintenance treatment of patients with locally advanced or metastatic, non-squamous NSCLC whose disease has not progressed after four cycles of platinum-based first-line chemotherapy.
- As a single agent for the treatment of patients with recurrent, metastatic non-squamous, NSCLC after prior chemotherapy.

Limitations of Use: Pemetrexed Injection is not indicated for the treatment of patients with squamous cell, non-small cell lung cancer [see Clinical Studies 14.1].

1.2 Mesothelioma

Pemetrexed Injection is indicated, in combination with cisplatin, for the initial treatment of patients with malignant pleural mesothelioma whose disease is unresectable or who are otherwise not candidates for curative surgery.

2 DOSAGE AND ADMINISTRATION

2.1 Recommended Dosage for Non-Squamous NSCLC

- The recommended dose of Pemetrexed Injection when administered with cisplatin for initial treatment of locally advanced or metastatic non-squamous NSCLC in patients with a creatinine clearance (calculated by Cockcroft-Gault equation) of 45 mL/min or greater is 500 mg/m^2 as an intravenous infusion over 10 minutes administered prior to cisplatin on Day 1 of each 21-day cycle for up to six cycles in the absence of disease progression or unacceptable toxicity.
- The recommended dose of Pemetrexed Injection for maintenance treatment of non-squamous NSCLC in patients with a creatinine clearance (calculated by Cockcroft-Gault equation) of 45 mL/min or greater is 500 mg/m^2 as an intravenous infusion over 10 minutes on Day 1 of each 21-day cycle until disease progression or unacceptable toxicity after four cycles of platinum-based first-line chemotherapy.
- The recommended dose of Pemetrexed Injection for treatment of recurrent non-squamous NSCLC in patients with a creatinine clearance (calculated by Cockcroft-Gault equation) of 45 mL/min or greater is 500 mg/m^2 as an intravenous infusion over 10 minutes on Day 1 of each 21-day cycle until disease progression or unacceptable toxicity.

2.2 Recommended Dosage for Mesothelioma

The recommended dose of Pemetrexed Injection when administered with cisplatin in patients with a creatinine clearance (calculated by Cockcroft-Gault equation) of 45 mL/min or greater is 500 mg/m^2 as an intravenous infusion over 10 minutes on Day 1 of each 21-day cycle until disease progression or unacceptable toxicity.

2.3 Renal Impairment

Pemetrexed Injection dosing recommendations are provided for patients with a creatinine clearance (calculated by Cockcroft-Gault equation) of 45 mL/min or greater [see Dosage and Administration (2.1, 2.2)]. There is no recommended dose for patients whose creatinine clearance is less than 45 mL/min [see Use in Specific Populations (8.6)].

2.4 Premedication and Concomitant Medications to Mitigate Toxicity

Vitamin Supplementation

- Initiate folic acid 400 mcg to 1000 mcg orally once daily, beginning 7 days before the first dose of Pemetrexed Injection and continuing until 21 days after the last dose of Pemetrexed Injection [see Warnings and Precautions (5.1)].
- Administer vitamin B12, 1 mg intramuscularly, 1 week prior to the first dose of Pemetrexed Injection and every 3 cycles thereafter. Subsequent vitamin B12 injections may be given the same day as treatment with Pemetrexed Injection [see Warnings and Precautions (5.1)]. Do not substitute oral vitamin B12 for intramuscular vitamin B12.

Corticosteroids

- Administer dexamethasone 4 mg orally twice daily for three consecutive days, beginning the day before each Pemetrexed Injection administration.

2.5 Dosage Modification of Ibuprofen in Patients with Mild to Moderate Renal Impairment Receiving Pemetrexed Injection

In patients with creatinine clearances between 45 mL/min and 79 mL/min, modify administration of ibuprofen as follows [see Warnings and Precautions (5.6), Drug Interactions (7) and Clinical Pharmacology (12.3)]:

- Avoid administration of ibuprofen for 2 days before, the day of, and 2 days following administration of Pemetrexed Injection.
- Monitor patients more frequently for myelosuppression, renal, and gastrointestinal toxicity, if concomitant administration of ibuprofen cannot be avoided.

2.6 Dosage Modifications for Adverse Reactions

Obtain complete blood count on Days 1, 8, and 15 of each cycle. Assess creatinine clearance prior to each cycle. Do not administer Pemetrexed Injection if the creatinine clearance is less than 45 mL/min.

Delay initiation of the next cycle of Pemetrexed Injection until:

- Recovery of non-hematologic toxicity to Grade 0–2,
- Absolute neutrophil count (ANC) is 1500 cells/mm^3 or higher, and
- Platelet count is 100,000 cells/mm^3 or higher.

Upon recovery, modify the dosage of Pemetrexed Injection in the next cycle as specified in Table 1.

For dosing modifications for cisplatin, refer to the prescribing information for cisplatin.

Table 1: Recommended Dosage Modifications for Adverse Reactions [National Cancer Institute Common Toxicity Criteria for Adverse Events version 2 (NCI CTCAE v2)]
Toxicity in Most Recent Treatment Cycle | Pemetrexed Injection Dose Modification for Next Cycle
Myelosuppressive toxicity [see Warnings and Precautions (5.1)]
ANC less than 500/mm^3 and platelets greater than or equal to 50,000/mm^3 OR Platelet count less than 50,000/mm^3 without bleeding | 75% of previous dose
Platelet count less than 50,000/mm^3 with bleeding | 50% of previous dose
Recurrent Grade 3 or 4 myelosuppression after 2 dose reductions | Discontinue
Non-hematologic toxicity
Any Grade 3 or 4 toxicities EXCEPT mucositis or neurologic toxicity or diarrhea requiring hospitalization | 75% of previous dose
Grade 3 or 4 mucositis | 50% of previous dose
Renal toxicity [see Warnings and Precautions (5.2)] | Withhold until creatinine clearance is 45 mL/min or greater
Grade 3 or 4 neurologic toxicity | Permanently discontinue
Recurrent Grade 3 or 4 non-hematologic toxicity after 2 dose reductions | Permanently discontinue
Severe and life-threatening Skin Toxicity [see Warnings and Precautions (5.3)] | Permanently discontinue
Interstitial Pneumonitis [see Warnings and Precautions (5.4)] | Permanently discontinue

2.7 Preparation for Administration

Pemetrexed Injection is a hazardous drug. Follow applicable special handling and disposal procedures.^1

- Calculate the dose of Pemetrexed Injection and determine the number of vials needed.
- Withdraw the calculated dose of Pemetrexed Injection from the vial(s) and discard vial with any unused portion.
- Dilute Pemetrexed Injection with 0.9% Sodium Chloride Injection, USP (preservative-free) to achieve a total volume of 100 mL for intravenous infusion.
- Visually inspect for particulate matter and discoloration prior to administration. Discard if particulate matter or discoloration is observed.
- Administer Pemetrexed Injection as an intravenous infusion over 10 minutes.
- If not used immediately, store diluted product under refrigerated conditions [2°C to 8°C (36°F to 46°F)] for no more than 24 hours from the time of dilution. Discard after 24 hours.

3 DOSAGE FORMS AND STRENGTHS

Pemetrexed Injection is a clear colorless to pale yellow ready-to-dilute solution available in single-dose vials as follows:

- 100 mg/4 mL (25 mg/mL)
- 500 mg/20 mL (25 mg/mL)
- 1 g/40 mL (25 mg/mL)

4 CONTRAINDICATIONS

Pemetrexed Injection is contraindicated in patients with a history of severe hypersensitivity reaction to pemetrexed [see Adverse Reactions (6.1)].

5 WARNINGS AND PRECAUTIONS

5.1 Myelosuppression and Increased Risk of Myelosuppression without Vitamin Supplementation

Pemetrexed can cause severe myelosuppression resulting in a requirement for transfusions and which may lead to neutropenic infection. The risk of myelosuppression is increased in patients who do not receive vitamin supplementation. In Study JMCH, incidences of Grade 3–4 neutropenia (38% versus 23%), thrombocytopenia (9% versus 5%), febrile neutropenia (9% versus 0.6%), and neutropenic infection (6% versus 0) were higher in patients who received pemetrexed plus cisplatin without vitamin supplementation as compared to patients who were fully supplemented with folic acid and vitamin B12 prior to and throughout pemetrexed plus cisplatin treatment.

Initiate supplementation with oral folic acid and intramuscular vitamin B12 prior to the first dose of Pemetrexed Injection; continue vitamin supplementation during treatment and for 21 days after the last dose of Pemetrexed Injection to reduce the severity of hematologic and gastrointestinal toxicity of Pemetrexed Injection [see Dosage and Administration (2.4)]. Obtain a complete blood count at the beginning of each cycle. Do not administer Pemetrexed Injection until the ANC is at least 1500 cells/mm^3 and platelet count is at least 100,000 cells/mm^3. Permanently reduce Pemetrexed Injection in patients with an ANC of less than 500 cells/mm^3 or platelet count of less than 50,000 cells/mm^3 in previous cycles [see Dosage and Administration (2.6)].

In Studies JMDB and JMCH, among patients who received vitamin supplementation, incidence of Grade 3–4 neutropenia was 15% and 23%, the incidence of Grade 3–4 anemia was 6% and 4%, and incidence of Grade 3–4 thrombocytopenia was 4% and 5%, respectively. In Study JMCH, 18% of patients in the pemetrexed arm required red blood cell transfusions compared to 7% of patients in the cisplatin arm [see Adverse Reactions (6.1)]. In Studies JMEN, PARAMOUNT, and JMEI, where all patients received vitamin supplementation, incidence of Grade 3–4 neutropenia ranged from 3% to 5%, and incidence of Grade 3–4 anemia ranged from 3% to 5%.

5.2 Renal Failure

Pemetrexed can cause severe, and sometimes fatal, renal toxicity. The incidences of renal failure in clinical studies in which patients received pemetrexed with cisplatin were: 2.1% in Study JMDB and 2.2% in Study JMCH. The incidence of renal failure in clinical studies in which patients received pemetrexed as a single agent ranged from 0.4% to 0.6% (Studies JMEN, PARAMOUNT, and JMEI [see Adverse Reactions (6.1)]). Determine creatinine clearance before each dose and periodically monitor renal function during treatment with Pemetrexed Injection. Withhold Pemetrexed Injection in patients with a creatinine clearance of less than 45 mL/minute [see Dosage and Administration (2.3)].

5.3 Bullous and Exfoliative Skin Toxicity

Serious and sometimes fatal, bullous, blistering and exfoliative skin toxicity, including cases suggestive of Stevens-Johnson Syndrome/Toxic epidermal necrolysis can occur with pemetrexed. Permanently discontinue Pemetrexed Injection for severe and life-threatening bullous, blistering or exfoliating skin toxicity.

5.4 Interstitial Pneumonitis

Serious interstitial pneumonitis, including fatal cases, can occur with pemetrexed treatment. Withhold Pemetrexed Injection for acute onset of new or progressive unexplained pulmonary symptoms such as dyspnea, cough, or fever pending diagnostic evaluation. If pneumonitis is confirmed, permanently discontinue Pemetrexed Injection.

5.5 Radiation Recall

Radiation recall can occur with pemetrexed in patients who have received radiation weeks to years previously. Monitor patients for inflammation or blistering in areas of previous radiation treatment. Permanently discontinue Pemetrexed Injection for signs of radiation recall.

5.6 Increased Risk of Toxicity with Ibuprofen in Patients with Renal Impairment

Exposure to pemetrexed is increased in patients with mild to moderate renal impairment who take concomitant ibuprofen, increasing the risks of adverse reactions of pemetrexed. In patients with creatinine clearances between 45 mL/min and 79 mL/min, avoid administration of ibuprofen for 2 days before, the day of, and 2 days following administration of Pemetrexed Injection. If concomitant ibuprofen use cannot be avoided, monitor patients more frequently for Pemetrexed Injection adverse reactions, including myelosuppression, renal, and gastrointestinal toxicity [see Dosage and Administration (2.5), Drug Interactions (7), and Clinical Pharmacology (12.3)].

5.7 Embryo-Fetal Toxicity

Based on findings from animal studies and its mechanism of action, Pemetrexed Injection can cause fetal harm when administered to a pregnant woman. In animal reproduction studies, intravenous administration of pemetrexed to pregnant mice during the period of organogenesis was teratogenic, resulting in developmental delays and increased malformations at doses lower than the recommended human dose of 500 mg/m^2. Advise pregnant women of the potential risk to a fetus. Advise females of reproductive potential to use effective contraception during treatment with Pemetrexed Injection and for 6 months after the last dose. Advise males with female partners of reproductive potential to use effective contraception during treatment with Pemetrexed Injection and for 3 months after the last dose [see Use in Specific Populations (8.1, 8.3) and Clinical Pharmacology (12.1)].

6 ADVERSE REACTIONS

The following adverse reactions are discussed in greater detail in other sections of the labeling:

- Myelosuppression [see Warnings and Precautions (5.1)]
- Renal failure [see Warnings and Precautions (5.2)]
- Bullous and exfoliative skin toxicity [see Warnings and Precautions (5.3)]
- Interstitial pneumonitis [see Warnings and Precautions (5.4)]
- Radiation recall [see Warnings and Precautions (5.5)]

6.1 Clinical Trials Experience

Because clinical trials are conducted under widely varying conditions, adverse reactions rates cannot be directly compared to rates in other clinical trials and may not reflect the rates observed in clinical practice.

In clinical trials, the most common adverse reactions (incidence ≥20%) of pemetrexed, when administered as a single agent, are fatigue, nausea, and anorexia. The most common adverse reactions (incidence ≥20%) of pemetrexed, when administered in combination with cisplatin are vomiting, neutropenia, anemia, stomatitis/pharyngitis, thrombocytopenia, and constipation.

Non-Squamous NSCLC

Initial Treatment in Combination with Cisplatin

The safety of pemetrexed was evaluated in Study JMDB, a randomized (1:1), open-label, multicenter trial conducted in chemotherapy-naive patients with locally advanced or metastatic NSCLC. Patients received either pemetrexed 500 mg/m^2 intravenously and cisplatin 75 mg/m^2 intravenously on Day 1 of each 21-day cycle (n=839) or gemcitabine 1250 mg/m^2 intravenously on Days 1 and 8 and cisplatin 75 mg/m^2 intravenously on Day 1 of each 21-day cycle (n=830). All patients were fully supplemented with folic acid and vitamin B12.

Study JMDB excluded patients with an Eastern Cooperative Oncology Group Performance Status (ECOG PS of 2 or greater), uncontrolled third-space fluid retention, inadequate bone marrow reserve and organ function, or a calculated creatinine clearance less than 45 mL/min. Patients unable to stop using aspirin or other non-steroidal anti-inflammatory drugs or unable to take folic acid, vitamin B12 or corticosteroids were also excluded from the study.

The data described below reflect exposure to pemetrexed plus cisplatin in 839 patients in Study JMDB. Median age was 61 years (range 26–83 years); 70% of patients were men; 78% were White,16% were Asian, 2.9% were Hispanic or Latino, 2.1% were Black or African American, and <1% were other ethnicities; 36% had an ECOG PS 0. Patients received a median of 5 cycles of pemetrexed.

Table 2 provides the frequency and severity of adverse reactions that occurred in ≥5% of 839 patients receiving pemetrexed in combination with cisplatin in Study JMDB. Study JMDB was not designed to demonstrate a statistically significant reduction in adverse reaction rates for pemetrexed, as compared to the control arm, for any specified adverse reaction listed in Table 2.

Table 2: Adverse Reactions Occurring in ≥5% of Fully Vitamin-Supplemented Patients Receiving Pemetrexed in Combination with Cisplatin Chemotherapy in Study JMDB
Adverse Reaction [NCI CTCAE version 2.0] | Pemetrexed/Cisplatin (N=839) |  | Gemcitabine/Cisplatin (N=830)
 | All Grades (%) | Grade 3–4 (%) | All Grades (%) | Grade 3–4 (%)
All adverse reactions | 90 | 37 | 91 | 53
Laboratory
Hematologic
Anemia | 33 | 6 | 46 | 10
Neutropenia | 29 | 15 | 38 | 27
Thrombocytopenia | 10 | 4 | 27 | 13
Renal
Elevated creatinine | 10 | 1 | 7 | 1
Clinical
Constitutional symptoms
Fatigue | 43 | 7 | 45 | 5
Gastrointestinal
Nausea | 56 | 7 | 53 | 4
Vomiting | 40 | 6 | 36 | 6
Anorexia | 27 | 2 | 24 | 1
Constipation | 21 | 1 | 20 | 0
Stomatitis/pharyngitis | 14 | 1 | 12 | 0
Diarrhea | 12 | 1 | 13 | 2
Dyspepsia/heartburn | 5 | 0 | 6 | 0
Neurology
Sensory neuropathy | 9 | 0 | 12 | 1
Taste disturbance | 8 | 0 | 9 | 0
Dermatology/Skin
Alopecia | 12 | 0 | 21 | 1
Rash/Desquamation | 7 | 0 | 8 | 1

The following additional adverse reactions of pemetrexed were observed.

Incidence 1% to <5%
Body as a Whole — febrile neutropenia, infection, pyrexia
General Disorders — dehydration
Metabolism and Nutrition — increased AST, increased ALT
Renal — renal failure
Eye Disorder — conjunctivitis

Incidence <1%
Cardiovascular — arrhythmia
General Disorders — chest pain
Metabolism and Nutrition — increased GGT
Neurology — motor neuropathy

Maintenance Treatment Following First-line Non-Pemetrexed Containing Platinum-Based Chemotherapy

In Study JMEN, the safety of pemetrexed was evaluated in a randomized (2:1), placebo-controlled, multicenter trial conducted in patients with non-progressive locally advanced or metastatic NSCLC following four cycles of a first-line, platinum-based chemotherapy regimen. Patients received either pemetrexed 500 mg/m^2 or matching placebo intravenously every 21 days until disease progression or unacceptable toxicity. Patients in both study arms were fully supplemented with folic acid and vitamin B12.

Study JMEN excluded patients with an ECOG PS of 2 or greater, uncontrolled third-space fluid retention, inadequate bone marrow reserve and organ function, or a calculated creatinine clearance less than 45 mL/min. Patients unable to stop using aspirin or other non-steroidal anti-inflammatory drugs or unable to take folic acid, vitamin B12 or corticosteroids were also excluded from the study.

The data described below reflect exposure to pemetrexed in 438 patients in Study JMEN. Median age was 61 years (range 26–83 years), 73% of patients were men; 65% were White, 31% were Asian, 2.9% were Hispanic or Latino, and <2% were other ethnicities; 39% had an ECOG PS 0. Patients received a median of 5 cycles of pemetrexed and a relative dose intensity of pemetrexed of 96%. Approximately half the patients (48%) completed at least six, 21-day cycles and 23% completed ten or more 21-day cycles of pemetrexed.

Table 3 provides the frequency and severity of adverse reactions reported in ≥5% of the 438 pemetrexed-treated patients in Study JMEN.

Table 3: Adverse Reactions Occurring in ≥5% of Patients Receiving Pemetrexed in Study JMEN
Adverse Reaction [NCI CTCAE version 3.0] | Pemetrexed/Cisplatin (N=438) |  | Placebo (N=218)
 | All Grades (%) | Grade 3–4 (%) | All Grades (%) | Grade 3–4 (%)
All adverse reactions | 66 | 16 | 37 | 4
Laboratory
Hematologic
Anemia | 15 | 3 | 6 | 1
Neutropenia | 6 | 3 | 0 | 0
Hepatic
Increased ALT | 10 | 0 | 4 | 0
Increased AST | 8 | 0 | 4 | 0
Clinical
Constitutional symptoms
Fatigue | 25 | 5 | 11 | 1
Gastrointestinal
Nausea | 19 | 1 | 6 | 1
Anorexia | 19 | 2 | 5 | 0
Vomiting | 9 | 0 | 1 | 0
Mucositis/stomatitis | 7 | 1 | 2 | 0
Diarrhea | 5 | 1 | 3 | 0
Infection | 5 | 2 | 2 | 0
Neurology
Sensory neuropathy | 9 | 1 | 4 | 0
Dermatology/Skin
Rash/Desquamation | 10 | 0 | 3 | 0

The requirement for transfusions (9.5% versus 3.2%), primarily red blood cell transfusions, and for erythropoiesis stimulating agents (5.9% versus 1.8%) were higher in the pemetrexed arm compared to the placebo arm.

The following additional adverse reactions were observed in patients who received pemetrexed.

Incidence 1% to <5%
Dermatology/Skin — alopecia, pruritus/itching
Gastrointestinal — constipation
General Disorders — edema, fever
Hematologic — thrombocytopenia
Eye Disorder — ocular surface disease (including conjunctivitis), increased lacrimation

Incidence <1%
Cardiovascular — supraventricular arrhythmia
Dermatology/Skin — erythema multiforme
General Disorders — febrile neutropenia, allergic reaction/hypersensitivity
Neurology — motor neuropathy
Renal — renal failure

Maintenance Treatment Following First-line Pemetrexed Plus Platinum Chemotherapy

The safety of pemetrexed was evaluated in PARAMOUNT, a randomized (2:1), placebo-controlled study conducted in patients with non-squamous NSCLC with non-progressive (stable or responding disease) locally advanced or metastatic NSCLC following four cycles of pemetrexed in combination with cisplatin as first-line therapy for NSCLC. Patients were randomized to receive pemetrexed 500 mg/m^2 or matching placebo intravenously on Day 1 of each 21-day cycle until disease progression or unacceptable toxicity. Patients in both study arms received folic acid and vitamin B12 supplementation.

PARAMOUNT excluded patients with an ECOG PS of 2 or greater, uncontrolled third-space fluid retention, inadequate bone marrow reserve and organ function, or a calculated creatinine clearance less than 45 mL/min. Patients unable to stop using aspirin or other non-steroidal anti-inflammatory drugs or unable to take folic acid, vitamin B12 or corticosteroids were also excluded from the study.

The data described below reflect exposure to pemetrexed in 333 patients in PARAMOUNT. Median age was 61 years (range 32 to 83 years); 58% of patients were men; 94% were White, 4.8% were Asian, and <1% were Black or African American; 36% had an ECOG PS 0. The median number of maintenance cycles was 4 for pemetrexed and placebo arms. Dose reductions for adverse reactions occurred in 3.3% of patients in the pemetrexed arm and 0.6% in the placebo arm. Dose delays for adverse reactions occurred in 22% of patients in the pemetrexed arm and 16% in the placebo arm.

Table 4 provides the frequency and severity of adverse reactions reported in ≥5% of the 333 pemetrexed-treated patients in PARAMOUNT.

Table 4: Adverse Reactions Occurring in ≥5% of Patients Receiving Pemetrexed in PARAMOUNT
Adverse Reaction [NCI CTCAE version 3.0] | Pemetrexed (N=333) |  | Placebo (N=167)
Adverse Reaction [NCI CTCAE version 3.0] | All Grades (%) | Grade 3–4 (%) | All Grades (%) | Grade 3–4 (%)
All adverse reactions | 53 | 17 | 34 | 4.8
Laboratory
Hematologic
Anemia | 15 | 4.8 | 4.8 | 0.6
Neutropenia | 9 | 3.9 | 0.6 | 0
Clinical
Constitutional symptoms
Fatigue | 18 | 4.5 | 11 | 0.6
Gastrointestinal
Nausea | 12 | 0.3 | 2.4 | 0
Vomiting | 6 | 0 | 1.8 | 0
Mucositis/stomatitis | 5 | 0.3 | 2.4 | 0
General disorders
Edema | 5 | 0 | 3.6 | 0

The requirement for red blood cell (13% versus 4.8%) and platelet (1.5% versus 0.6%) transfusions, erythropoiesis stimulating agents (12% versus 7%), and granulocyte colony stimulating factors (6% versus 0%) were higher in the pemetrexed arm compared to the placebo arm.

The following additional Grade 3 or 4 adverse reactions were observed more frequently in the pemetrexed arm.

Incidence 1% to <5%
Blood/Bone Marrow — thrombocytopenia
General Disorders — febrile neutropenia

Incidence <1%
Cardiovascular — ventricular tachycardia, syncope
General Disorders — pain
Gastrointestinal — gastrointestinal obstruction
Neurologic — depression
Renal — renal failure
Vascular — pulmonary embolism

Treatment of Recurrent Disease After Prior Chemotherapy

The safety of pemetrexed was evaluated in Study JMEI, a randomized (1:1), open-label, active-controlled trial conducted in patients who had progressed following platinum-based chemotherapy. Patients received pemetrexed 500 mg/m^2 intravenously or docetaxel 75 mg/m^2 intravenously on Day 1 of each 21-day cycle. All patients on the pemetrexed arm received folic acid and vitamin B12 supplementation.

Study JMEI excluded patients with an ECOG PS of 3 or greater, uncontrolled third-space fluid retention, inadequate bone marrow reserve and organ function, or a calculated creatinine clearance less than 45 mL/min. Patients unable to discontinue aspirin or other non-steroidal anti-inflammatory drugs or unable to take folic acid, vitamin B12 or corticosteroids were also excluded from the study.

The data described below reflect exposure to pemetrexed in 265 patients in Study JMEI. Median age was 58 years (range 22 to 87 years); 73% of patients were men; 70% were White, 24% were Asian, 2.6% were Black or African American, 1.8% were Hispanic or Latino, and <2% were other ethnicities; 19% had an ECOG PS 0.

Table 5 provides the frequency and severity of adverse reactions reported in ≥5% of the 265 pemetrexed-treated patients in Study JMEI. Study JMEI is not designed to demonstrate a statistically significant reduction in adverse reaction rates for pemetrexed, as compared to the control arm, for any specified adverse reaction listed in the Table 5 below.

Table 5: Adverse Reactions Occurring in ≥5% of Fully Supplemented Patients Receiving Pemetrexed in Study JMEI
Adverse Reaction [NCI CTCAE version 2.0] | Pemetrexed (N=265) |  | Docetaxel (N=276)
 | All Grades (%) | Grade 3–4 (%) | All Grades (%) | Grade 3–4 (%)
Laboratory
Hematologic
Anemia | 19 | 4 | 22 | 4
Neutropenia | 11 | 5 | 45 | 40
Thrombocytopenia | 8 | 2 | 1 | 0
Hepatic
Increased ALT | 8 | 2 | 1 | 0
Increased AST | 7 | 1 | 1 | 0
Clinical
Gastrointestinal
Nausea | 31 | 3 | 17 | 2
Anorexia | 22 | 2 | 24 | 3
Vomiting | 16 | 2 | 12 | 1
Stomatitis/pharyngitis | 15 | 1 | 17 | 1
Diarrhea | 13 | 0 | 24 | 3
Constipation | 6 | 0 | 4 | 0
Constitutional symptoms
Fatigue | 34 | 5 | 36 | 5
Fever | 8 | 0 | 8 | 0
Dermatology/Skin
Rash/desquamation | 14 | 0 | 6 | 0
Pruritus | 7 | 0 | 2 | 0
Alopecia | 6 | 1 | 38 | 2

The following additional adverse reactions were observed in patients assigned to receive pemetrexed.

Incidence 1% to <5%
Body as a Whole — abdominal pain, allergic reaction/hypersensitivity, febrile neutropenia, infection
Dermatology/Skin — erythema multiforme
Neurology — motor neuropathy, sensory neuropathy

Incidence <1%
Cardiovascular — supraventricular arrhythmias
Renal — renal failure

Mesothelioma

The safety of pemetrexed was evaluated in Study JMCH, a randomized (1:1), single-blind study conducted in patients with MPM who had received no prior chemotherapy for MPM. Patients received pemetrexed 500 mg/m^2 intravenously in combination with cisplatin 75 mg/m^2 intravenously on Day 1 of each 21-day cycle or cisplatin 75 mg/m^2 intravenously on Day 1 of each 21-day cycle administered until disease progression or unacceptable toxicity. Safety was assessed in 226 patients who received at least one dose of pemetrexed in combination with cisplatin and 222 patients who received at least one dose of cisplatin alone. Among 226 patients who received pemetrexed in combination with cisplatin, 74% (n=168) received full supplementation with folic acid and vitamin B12 during study therapy, 14% (n=32) were never supplemented, and 12% (n=26) were partially supplemented.

Study JMCH excluded patients with Karnofsky Performance Scale (KPS) of less than 70, inadequate bone marrow reserve and organ function, or a calculated creatinine clearance less than 45 mL/min. Patients unable to stop using aspirin or other non-steroidal anti-inflammatory drugs were also excluded from the study.

The data described below reflect exposure to pemetrexed in 168 patients that were fully supplemented with folic acid and vitamin B12. Median age was 60 years (range 19 to 85 years); 82% were men; 92% were White, 5% were Hispanic or Latino, 3.0% were Asian, and <1% were other ethnicities; 54% had KPS of 90–100. The median number of treatment cycles administered was 6 in the pemetrexed/cisplatin fully supplemented group and 2 in the pemetrexed/cisplatin never supplemented group. Patients receiving pemetrexed in the fully supplemented group had a relative dose intensity of 93% of the protocol-specified pemetrexed dose intensity. The most common adverse reaction resulting in dose delay was neutropenia.

Table 6 provides the frequency and severity of adverse reactions ≥5% in the subgroup of pemetrexed-treated patients who were fully vitamin supplemented in Study JMCH. Study JMCH was not designed to demonstrate a statistically significant reduction in adverse reaction rates for pemetrexed, as compared to the control arm, for any specified adverse reaction listed in the table below.

Table 6: Adverse Reactions Occurring in ≥5% of Fully Supplemented Subgroup of Patients Receiving Pemetrexed/Cisplatin in Study JMCH [In Study JMCH, 226 patients received at least one dose of pemetrexed in combination with cisplatin and 222 patients received at least one dose of cisplatin. Table 6 provides the ADRs for subgroup of patients treated with pemetrexed in combination with cisplatin (168 patients) or cisplatin alone (163 patients) who received full supplementation with folic acid and vitamin B12 during study therapy.]
Adverse Reaction [NCI CTCAE version 2.0] | Pemetrexed/cisplatin (N=168) |  | Cisplatin (N=163)
Adverse Reaction [NCI CTCAE version 2.0] | All Grades (%) | Grade 3–4 (%) | All Grades (%) | Grade 3–4 (%)
Laboratory
Hematologic
Neutropenia | 56 | 23 | 13 | 3
Anemia | 26 | 4 | 10 | 0
Thrombocytopenia | 23 | 5 | 9 | 0
Renal
Elevated creatinine | 11 | 1 | 10 | 1
Decreased creatinine clearance | 16 | 1 | 18 | 2
Clinical
Eye Disorder
Conjunctivitis | 5 | 0 | 1 | 0
Gastrointestinal
Nausea | 82 | 12 | 77 | 6
Vomiting | 57 | 11 | 50 | 4
Stomatitis/pharyngitis | 23 | 3 | 6 | 0
Anorexia | 20 | 1 | 14 | 1
Diarrhea | 17 | 4 | 8 | 0
Constipation | 12 | 1 | 7 | 1
Dyspepsia | 5 | 1 | 1 | 0
Constitutional Symptoms
Fatigue | 48 | 10 | 42 | 9
Metabolism and Nutrition
Dehydration | 7 | 4 | 1 | 1
Neurology
Sensory neuropathy | 10 | 0 | 10 | 1
Taste disturbance | 8 | 0 | 6 | 0
Dermatology/Skin
Rash | 16 | 1 | 5 | 0
Alopecia | 11 | 0 | 6 | 0

The following additional adverse reactions were observed in patients receiving pemetrexed plus cisplatin:

Incidence 1% to <5%
Body as a Whole — febrile neutropenia, infection, pyrexia
Dermatology/Skin — urticaria
General Disorders — chest pain
Metabolism and Nutrition — increased AST, increased ALT, increased GGT
Renal — renal failure

Incidence <1%
Cardiovascular — arrhythmia
Neurology — motor neuropathy

Exploratory Subgroup Analyses based on Vitamin Supplementation

Table 7 provides the results of exploratory analyses of the frequency and severity of NCI CTCAE Grade 3 or 4 adverse reactions reported in more pemetrexed-treated patients who did not receive vitamin supplementation (never supplemented) as compared with those who received vitamin supplementation with daily folic acid and vitamin B12 from the time of enrollment in Study JMCH (fully supplemented).

Table 7: Exploratory Subgroup Analysis of Selected Grade 3/4 Adverse Reactions Occurring in Patients Receiving Pemetrexed in Combination with Cisplatin with or without Full Vitamin Supplementation in Study JMCH [NCI CTCAE version 2.0]
Grade 3–4 Adverse Reactions | Fully Supplemented Patients N=168 (%) | Never Supplemented Patients N=32 (%)
Neutropenia | 23 | 38
Thrombocytopenia | 5 | 9
Vomiting | 11 | 31
Febrile neutropenia | 1 | 9
Infection with Grade 3/4 neutropenia | 0 | 6
Diarrhea | 4 | 9

The following adverse reactions occurred more frequently in patients who were fully vitamin supplemented than in patients who were never supplemented:

- hypertension (11% versus 3%),
- chest pain (8% versus 6%),
- thrombosis/embolism (6% versus 3%).

Additional Experience Across Clinical Trials

Sepsis, with or without neutropenia, including fatal cases: 1%
Severe esophagitis, resulting in hospitalization: <1%

6.2 Postmarketing Experience

The following adverse reactions have been identified during post-approval use of pemetrexed. Because these reactions are reported voluntarily from a population of uncertain size, it is not always possible to reliably estimate their frequency or establish a causal relationship to drug exposure.

Blood and Lymphatic System — immune-mediated hemolytic anemia
Gastrointestinal — colitis, pancreatitis
General Disorders and Administration Site Conditions — edema
Injury, Poisoning, and Procedural Complications — radiation recall
Respiratory — interstitial pneumonitis
Skin — Serious and fatal bullous skin conditions, Stevens-Johnson syndrome, and toxic epidermal necrolysis

7 DRUG INTERACTIONS

Effects of Ibuprofen on Pemetrexed

Ibuprofen increases exposure (AUC) of pemetrexed [see Clinical Pharmacology (12.3)]. In patients with creatinine clearance between 45 mL/min and 79 mL/min:

- Avoid administration of ibuprofen for 2 days before, the day of, and 2 days following administration of Pemetrexed Injection [see Dosage and Administration (2.5)].
- Monitor patients more frequently for myelosuppression, renal, and gastrointestinal toxicity, if concomitant administration of ibuprofen cannot be avoided.

8 USE IN SPECIFIC POPULATIONS

8.1 Pregnancy

Risk Summary

Based on findings from animal studies and its mechanism of action, Pemetrexed Injection can cause fetal harm when administered to a pregnant woman [see Clinical Pharmacology (12.1)]. There are no available data on Pemetrexed Injection use in pregnant women. In animal reproduction studies, intravenous administration of pemetrexed to pregnant mice during the period of organogenesis was teratogenic, resulting in developmental delays and malformations at doses lower than the recommended human dose of 500 mg/m^2 [see Data]. Advise pregnant women of the potential risk to a fetus [see Use in Special Populations (8.3)].

In the U.S. general population, the estimated background risk of major birth defects and miscarriage in clinically recognized pregnancies is 2 to 4% and 15 to 20%, respectively.

Data

Animal Data

Pemetrexed was teratogenic in mice. Daily dosing of pemetrexed by intravenous injection to pregnant mice during the period of organogenesis increased the incidence of fetal malformations (cleft palate; protruding tongue; enlarged or misshaped kidney; and fused lumbar vertebra) at doses (based on BSA) 0.03 times the human dose of 500 mg/m^2. At doses, based on BSA, greater than or equal to 0.0012 times the 500 mg/m^2 human dose, pemetrexed administration resulted in dose-dependent increases in developmental delays (incomplete ossification of talus and skull bone; and decreased fetal weight).

8.2 Lactation

Risk Summary

There is no information regarding the presence of pemetrexed or its metabolites in human milk, the effects on the breastfed infant, or the effects on milk production. Because of the potential for serious adverse reactions in breastfed infants from Pemetrexed Injection, advise women not to breastfeed during treatment with Pemetrexed Injection and for one week after last dose.

8.3 Females and Males of Reproductive Potential

Based on animal data, pemetrexed can cause malformations and developmental delays when administered to a pregnant woman [see Use in Specific Populations (8.1)].

Pregnancy Testing

Verify pregnancy status of females of reproductive potential prior to initiating Pemetrexed Injection [see Use in Specific Populations (8.1)].

Contraception

Females

Because of the potential for genotoxicity, advise females of reproductive potential to use effective contraception during treatment with Pemetrexed Injection and for 6 months after the last dose of Pemetrexed Injection.

Males

Because of the potential for genotoxicity, advise males with female partners of reproductive potential to use effective contraception during treatment with Pemetrexed Injection and for 3 months after the last dose [see Nonclinical Toxicology (13.1)].

Infertility

Males

Pemetrexed Injection may impair fertility in males of reproductive potential. It is not known whether these effects on fertility are reversible [see Nonclinical Toxicology (13.1)].

8.4 Pediatric Use

The safety and effectiveness of Pemetrexed Injection in pediatric patients have not been established.

The safety and pharmacokinetics of pemetrexed were evaluated in two clinical studies conducted in pediatric patients with recurrent solid tumors (NCT00070473, N=32 and NCT00520936, N=72). Patients in both studies received concomitant vitamin B12 and folic acid supplementation and dexamethasone.

No tumor responses were observed. Adverse reactions observed in pediatric patients were similar to those observed in adults.

Pharmacokinetics of pemetrexed in 22 patients age 4 to 18 years enrolled in NCT00070473 were within range of values in adults.

8.5 Geriatric Use

Of the 3,946 patients enrolled in clinical studies of pemetrexed, 34% were 65 and over and 4% were 75 and over. No overall differences in effectiveness were observed between these patients and younger patients. The incidences of Grade 3–4 anemia, fatigue, thrombocytopenia, hypertension, and neutropenia were higher in patients 65 years of age and older as compared to younger patients: in at least one of five randomized clinical trials. [see Adverse Reactions (6.1) and Clinical Studies (14.1, 14.2)].

8.6 Patients with Renal Impairment

Pemetrexed is primarily excreted by the kidneys. Decreased renal function results in reduced clearance and greater exposure (AUC) to pemetrexed compared with patients with normal renal function [Warnings and Precautions (5.2, 5.6) and Clinical Pharmacology (12.3)]. No dose is recommended for patients with creatinine clearance less than 45 mL/min [see Dosage and Administration (2.3)].

10 OVERDOSAGE

No drugs are approved for the treatment of Pemetrexed Injection overdose. Based on animal studies, administration of leucovorin may mitigate the toxicities of Pemetrexed Injection overdosage. It is not known whether pemetrexed is dialyzable.

11 DESCRIPTION

Pemetrexed is a folate analog metabolic inhibitor. The drug substance, pemetrexed disodium (2.5 H2O), has the chemical name N-[[4-[2-(2-Amino-4-oxo-4,7-dihydro-1H-pyrrolo[2,3-d]pyrimidin-5-yl)ethyl]phenyl]carbonyl]-L-glutamic acid disodium, hemipentahydrate with a molecular formula of C20H19N5Na2O6 ∙2.5H2O and a molecular weight of 516.41. The structural formula is as follows:

Pemetrexed Injection, 100 mg/4 mL, 500 mg/20 mL, and 1 g/40 mL are supplied as a sterile, preservative-free, clear, colorless to pale yellow ready-to-dilute solution in a single-dose vial for intravenous infusion. Each milliliter (mL) contains 25 mg pemetrexed (equivalent to 27.57 mg pemetrexed disodium), 1.2 mg monothioglycerol, water for injection and may contain sodium hydroxide for pH adjustment.

12 CLINICAL PHARMACOLOGY

12.1 Mechanism of Action

Pemetrexed Injection is a folate analog metabolic inhibitor that disrupts folate-dependent metabolic processes essential for cell replication. In vitro studies show that pemetrexed inhibits thymidylate synthase (TS), dihydrofolate reductase, and glycinamide ribonucleotide formyltransferase (GARFT), which are folate-dependent enzymes involved in the de novo biosynthesis of thymidine and purine nucleotides. Pemetrexed is taken into cells by membrane carriers such as the reduced folate carrier and membrane folate binding protein transport systems. Once in the cell, pemetrexed is converted to polyglutamate forms by the enzyme folylpolyglutamate synthetase. The polyglutamate forms are retained in cells and are inhibitors of TS and GARFT.

12.2 Pharmacodynamics

Pemetrexed inhibited the in vitro growth of mesothelioma cell lines (MSTO-211H, NCI-H2052) and showed synergistic effects when combined with cisplatin.

Based on population pharmacodynamic analyses, the depth of the absolute neutrophil counts (ANC) nadir correlates with the systemic exposure to pemetrexed and supplementation with folic acid and vitamin B12. There is no cumulative effect of pemetrexed exposure on ANC nadir over multiple treatment cycles.

12.3 Pharmacokinetics

Absorption

The pharmacokinetics of pemetrexed when pemetrexed was administered as a single agent in doses ranging from 0.2 to 838 mg/m^2 infused over a 10-minute period have been evaluated in 426 cancer patients with a variety of solid tumors. Pemetrexed total systemic exposure (AUC) and maximum plasma concentration (Cmax) increased proportionally with increase of dose. The pharmacokinetics of pemetrexed did not change over multiple treatment cycles.

Distribution

Pemetrexed has a steady-state volume of distribution of 16.1 liters. In vitro studies indicated that pemetrexed is 81% bound to plasma proteins.

Elimination

The total systemic clearance of pemetrexed is 91.8 mL/min and the elimination half-life of pemetrexed is 3.5 hours in patients with normal renal function (creatinine clearance of 90 mL/min). As renal function decreases, the clearance of pemetrexed decreases and exposure (AUC) of pemetrexed increases.

Metabolism

Pemetrexed is not metabolized to an appreciable extent.

Excretion

Pemetrexed is primarily eliminated in the urine, with 70% to 90% of the dose recovered unchanged within the first 24 hours following administration. In vitro studies indicated that pemetrexed is a substrate of OAT3 (organic anion transporter 3), a transporter that is involved in the active secretion of pemetrexed.

Specific Populations

Age (26 to 80 years) and sex had no clinically meaningful effect on the systemic exposure of pemetrexed based on population pharmacokinetic analyses.

Racial Groups

The pharmacokinetics of pemetrexed were similar in Whites and Blacks or African Americans. Insufficient data are available for other ethnic groups.

Patients with Hepatic Impairment

Pemetrexed has not been formally studied in patients with hepatic impairment. No effect of elevated AST, ALT, or total bilirubin on the PK of pemetrexed was observed in clinical studies.

Patients with Renal Impairment

Pharmacokinetic analyses of pemetrexed included 127 patients with impaired renal function. Plasma clearance of pemetrexed decreases as renal function decreases, with a resultant increase in systemic exposure. Patients with creatinine clearances of 45, 50, and 80 mL/min had 65%, 54%, and 13% increases, respectively in systemic exposure (AUC) compared to patients with creatinine clearance of 100 mL/min [see Dosage and Administration (2.3) and Warnings and Precautions (5.2)].

Third-Space Fluid

The pemetrexed plasma concentrations in patients with various solid tumors with stable, mild to moderate third-space fluid were comparable to those observed in patients without third-space fluid collections. The effect of severe third-space fluid on pharmacokinetics is not known.

Drug Interaction Studies

Drugs Inhibiting OAT3 Transporter

Ibuprofen, an OAT3 inhibitor, administered at 400 mg four times a day decreased the clearance of pemetrexed and increased its exposure (AUC) by approximately 20% in patients with normal renal function (creatinine clearance >80 mL/min).

In Vitro Studies

Pemetrexed is a substrate for OAT3. Ibuprofen, an OAT3 inhibitor inhibited the uptake of pemetrexed in OAT3-expressing cell cultures with an average [Iu]/IC50 ratio of 0.38. In vitro data predict that at clinically relevant concentrations, other NSAIDs (naproxen, diclofenac, celecoxib) would not inhibit the uptake of pemetrexed by OAT3 and would not increase the AUC of pemetrexed to a clinically significant extent [see Drug Interactions (7)].

Pemetrexed is a substrate for OAT4. In vitro, ibuprofen and other NSAIDs (naproxen, diclofenac, celecoxib) are not inhibitors of OAT4 at clinically relevant concentrations.

Aspirin

Aspirin, administered in low to moderate doses (325 mg every 6 hours), does not affect the pharmacokinetics of pemetrexed.

Cisplatin

Cisplatin does not affect the pharmacokinetics of pemetrexed and the pharmacokinetics of total platinum are unaltered by pemetrexed.

Vitamins

Neither folic acid nor vitamin B12 affect the pharmacokinetics of pemetrexed.

Drugs Metabolized by Cytochrome P450 Enzymes

In vitro studies suggest that pemetrexed does not inhibit the clearance of drugs metabolized by CYP3A, CYP2D6, CYP2C9, and CYP1A2.

13 NONCLINICAL TOXICOLOGY

13.1 Carcinogenesis, Mutagenesis, Impairment of Fertility

No carcinogenicity studies have been conducted with pemetrexed. Pemetrexed was clastogenic in an in vivo micronucleus assay in mouse bone marrow but was not mutagenic in multiple in vitro tests (Ames assay, Chinese Hamster Ovary cell assay).

Pemetrexed administered intraperitoneally at doses of ≥0.1 mg/kg/day to male mice (approximately 0.0006 times the recommended human dose based on BSA) resulted in reduced fertility, hypospermia, and testicular atrophy.

14 CLINICAL STUDIES

14.1 Non-Squamous NSCLC

Initial Treatment in Combination with Cisplatin

The efficacy of pemetrexed was evaluated in Study JMDB (NCT00087711), a multi-center, randomized (1:1), open-label study conducted in 1725 chemotherapy-naive patients with Stage IIIb/IV NSCLC. Patients were randomized to receive pemetrexed with cisplatin or gemcitabine with cisplatin. Randomization was stratified by Eastern Cooperative Oncology Group Performance Status (ECOG PS 0 versus 1), gender, disease stage, basis for pathological diagnosis (histopathological/cytopathological), history of brain metastases, and investigative center. Pemetrexed was administered intravenously over 10 minutes at a dose of 500 mg/m^2 on Day 1 of each 21-day cycle. Cisplatin was administered intravenously at a dose of 75 mg/m^2 approximately 30 minutes after pemetrexed administration on Day 1 of each cycle, gemcitabine was administered at a dose of 1250 mg/m^2 on Day 1 and Day 8, and cisplatin was administered intravenously at a dose of 75 mg/m^2 approximately 30 minutes after administration of gemcitabine, on Day 1 of each 21-day cycle. Treatment was administered up to a total of 6 cycles; patients in both arms received folic acid, vitamin B12, and dexamethasone [see Dosage and Administration (2.4)]. The primary efficacy outcome measure was overall survival.

A total of 1725 patients were enrolled with 862 patients randomized to pemetrexed in combination with cisplatin and 863 patients to gemcitabine in combination with cisplatin. The median age was 61 years (range 26–83 years), 70% were male, 78% were White, 17% were Asian, 2.9% were Hispanic or Latino, and 2.1% were Black or African American, and <1% were other ethnicities. Among patients for whom ECOG PS (n=1722) and smoking history (n=1516) were collected, 65% had an ECOG PS of 1, 36% had an ECOG PS of 0, and 84% were smokers. For tumor characteristics, 73% had non-squamous NSCLC and 27% had squamous NSCLC; 76% had Stage IV disease. Among 1252 patients with non-squamous NSCLC histology, 68% had a diagnosis of adenocarcinoma, 12% had large cell histology and 20% had other histologic subtypes.

Efficacy results in Study JMDB are presented in Table 8 and Figure 1.

Table 8: Efficacy Results in Study JMDB
Efficacy Parameter | Pemetrexed plus Cisplatin (N=862) | Gemcitabine plus Cisplatin (N=863)
Overall Survival
Median (months) | 10.3 | 10.3
(95% CI) | (9.8–11.2) | (9.6–10.9)
Hazard ratio (HR) [Unadjusted for multiple comparisons.] , [Adjusted for gender, stage, basis of diagnosis, and performance status.] | 0.94
(95% CI) | (0.84–1.05)
Progression-Free Survival
Median (months) | 4.8 | 5.1
(95% CI) | (4.6–5.3) | (4.6–5.5)
Hazard ratio (HR), | 1.04
(95% CI) | (0.94–1.15)
Overall Response Rate | 27.1% | 24.7%
(95% CI) | (24.2–30.1) | (21.8–27.6)

Figure 1: Kaplan-Meier Curves for Overall Survival in Study JMDB

In pre-specified analyses assessing the impact of NSCLC histology on overall survival, clinically relevant differences in survival according to histology were observed. These subgroup analyses are shown in Table 9 and Figures 2 and 3. This difference in treatment effect for pemetrexed based on histology demonstrating a lack of efficacy in squamous cell histology was also observed in Studies JMEN and JMEI.

Table 9: Overall Survival in NSCLC Histologic Subgroups in Study JMDB
Histologic Subgroups | Pemetrexed plus Cisplatin (N=862) | Gemcitabine plus Cisplatin (N=863)
Non-squamous NSCLC (N=1252)
Median (months) | 11.0 | 10.1
(95% CI) | (10.1–12.5) | (9.3–10.9)
HR [Unadjusted for multiple comparisons.] , [Adjusted for ECOG PS, gender, disease stage, and basis for pathological diagnosis (histopathological/cytopathological).] | 0.84
(95% CI) | (0.74–0.96)
Adenocarcinoma (N=847)
Median (months) | 12.6 | 10.9
(95% CI) | (10.7–13.6) | (10.2–11.9)
HR, | 0.84
(95% CI) | (0.71–0.99)
Large Cell (N=153)
Median (months) | 10.4 | 6.7
(95% CI) | (8.6–14.1) | (5.5–9.0)
HR, | 0.67
(95% CI) | (0.48–0.96)
Non-squamous, not otherwise specified (N=252)
Median (months) | 8.6 | 9.2
(95% CI) | (6.8–10.2) | (8.1–10.6)
HR, | 1.08
(95% CI) | (0.81–1.45)
Squamous Cell (N=473)
Median (months) | 9.4 | 10.8
(95% CI) | (8.4–10.2) | (9.5–12.1)
HR, | 1.23
(95% CI) | (1.00–1.51)

Figure 2: Kaplan-Meier Curves for Overall Survival in Non-squamous NSCLC in Study JMDB

Figure 3: Kaplan-Meier Curves for Overall Survival in Squamous NSCLC in Study JMDB

Maintenance Treatment Following First-line Non-Pemetrexed Containing Platinum-Based Chemotherapy

The efficacy of pemetrexed as maintenance therapy following first-line platinum-based chemotherapy was evaluated in Study JMEN (NCT00102804), a multicenter, randomized (2:1), double-blind, placebo-controlled study conducted in 663 patients with Stage IIIb/IV NSCLC who did not progress after four cycles of platinum-based chemotherapy. Patients were randomized to receive pemetrexed 500 mg/m^2 intravenously every 21 days or placebo until disease progression or intolerable toxicity. Patients in both study arms received folic acid, vitamin B12, and dexamethasone [see Dosage and Administration (2.4)]. Randomization was carried out using a minimization approach [Pocock and Simon (1975)] using the following factors: gender, ECOG PS (0 versus 1), response to prior chemotherapy (complete or partial response versus stable disease), history of brain metastases (yes versus no), non-platinum component of induction therapy (docetaxel versus gemcitabine versus paclitaxel), and disease stage (IIIb versus IV). The major efficacy outcome measures were progression-free survival based on assessment by independent review and overall survival; both were measured from the date of randomization in Study JMEN.

A total of 663 patients were enrolled with 441 patients randomized to pemetrexed and 222 patients randomized to placebo. The median age was 61 years (range 26–83 years); 73% were male; 65% were White, 32% were Asian, 2.9% were Hispanic or Latino, and <2% were other ethnicities; 60% had an ECOG PS of 1; and 73% were current or former smokers. Median time from initiation of platinum-based chemotherapy to randomization was 3.3 months (range 1.6 to 5.1 months) and 49% of the population achieved a partial or complete response to first-line, platinum-based chemotherapy. With regard to tumor characteristics, 81% had Stage IV disease, 73% had non-squamous NSCLC and 27% had squamous NSCLC. Among the 481 patients with non-squamous NSCLC, 68% had adenocarcinoma, 4% had large cell, and 28% had other histologies.

Efficacy results are presented in Table 10 and Figure 4.

Table 10: Efficacy Results in Study JMEN
Efficacy Parameter | Pemetrexed | Placebo
Overall survival | N=441 | N=222
Median (months) | 13.4 | 10.6
(95% CI) | (11.9–15.9) | (8.7–12.0)
Hazard ratio [Hazard ratios are adjusted for multiplicity but not for stratification variables.] | 0.79
(95% CI) | (0.65–0.95)
p-value | p=0.012
Progression-free survival per independent review | N=387 | N=194
Median (months) | 4.0 | 2.0
(95% CI) | (3.1–4.4) | (1.5–2.8)
Hazard ratio | 0.60
(95% CI) | (0.49–0.73)
p-value | p<0.00001

Figure 4: Kaplan-Meier Curves for Overall Survival in Study JMEN

The results of pre-specified subgroup analyses by NSCLC histology are presented in Table 11 and Figures 5 and 6.

Table 11: Efficacy Results in Study JMEN by Histologic Subgroup
Efficacy Parameter | Overall Survival |  | Progression-Free Survival Per Independent Review
 | Pemetrexed (N=441) | Placebo (N=222) | Pemetrexed (N=387) | Placebo (N=194)
Non-squamous NSCLC (n=481)
Median (months) | 15.5 | 10.3 | 4.4 | 1.8
HR [Hazard ratios are not adjusted for multiplicity] | 0.70 |  | 0.47
(95% CI) | (0.56–0.88) |  | (0.37–0.60)
Adenocarcinoma (n=328)
Median (months) | 16.8 | 11.5 | 4.6 | 2.7
HR | 0.73 |  | 0.51
(95% CI) | (0.56–0.96) |  | (0.38–0.68)
Large cell carcinoma (n=20)
Median (months) | 8.4 | 7.9 | 4.5 | 1.5
HR | 0.98 |  | 0.40
(95% CI) | (0.36–2.65) |  | (0.12–1.29)
Other [Primary diagnosis of NSCLC not specified as adenocarcinoma, large cell carcinoma, or squamous cell carcinoma.] (n=133)
Median (months) | 11.3 | 7.7 | 4.1 | 1.6
HR | 0.61 |  | 0.44
(95% CI) | (0.40–0.94) |  | (0.28–0.68)
Squamous cell NSCLC (n=182)
Median (months) | 9.9 | 10.8 | 2.4 | 2.5
HR | 1.07 |  | 1.03
(95% CI) | (0.77–1.50) |  | (0.71–1.49)

Figure 5: Kaplan-Meier Curves for Overall Survival in Non-squamous NSCLC in Study JMEN

Figure 6: Kaplan-Meier Curves for Overall Survival in Squamous NSCLC in Study JMEN

Maintenance Treatment Following First-line Pemetrexed Plus Platinum Chemotherapy

The efficacy of pemetrexed as maintenance therapy following first-line platinum-based chemotherapy was also evaluated in PARAMOUNT (NCT00789373), a multi-center, randomized (2:1), double-blind, placebo-controlled study conducted in patients with Stage IIIb/IV non-squamous NSCLC who had completed four cycles of pemetrexed in combination with cisplatin and achieved a complete response (CR) or partial response (PR) or stable disease (SD). Patients were required to have an ECOG PS of 0 or 1. Patients were randomized to receive pemetrexed 500 mg/m^2 intravenously every 21 days or placebo until disease progression. Randomization was stratified by response to pemetrexed in combination with cisplatin induction therapy (CR or PR versus SD), disease stage (IIIb versus IV), and ECOG PS (0 versus 1). Patients in both arms received folic acid, vitamin B12, and dexamethasone. The main efficacy outcome measure was investigator-assessed progression-free survival (PFS) and an additional efficacy outcome measure was overall survival (OS); PFS and OS were measured from the time of randomization.

A total of 539 patients were enrolled with 359 patients randomized to pemetrexed and 180 patients randomized to placebo. The median age was 61 years (range 32 to 83 years); 58% were male; 95% were White, 4.5% were Asian, and <1% were Black or African American; 67% had an ECOG PS of 1; 78% were current or former smokers; and 43% of the population achieved a partial or complete response to first-line, platinum-based chemotherapy. With regard to tumor characteristics, 91% had Stage IV disease, 87% had adenocarcinoma, 7% had large cell, and 6% had other histologies.

Efficacy results for PARAMOUNT are presented in Table 12 and Figure 7.

Table 12: Efficacy Results in PARAMOUNT
Efficacy Parameter | Pemetrexed (N=359) | Placebo (N=180)
Overall survival
Median (months) | 13.9 | 11.0
(95% CI) | (12.8–16.0) | (10.0–12.5)
Hazard ratio (HR) [Hazard ratios are adjusted for multiplicity but not for stratification variables.] | 0.78
(95% CI) | (0.64–0.96)
p-value | p=0.02
Progression-free survival [Based on investigator's assessment.]
Median (months) | 4.1 | 2.8
(95% CI) | (3.2–4.6) | (2.6–3.1)
Hazard ratio (HR) | 0.62
(95% CI) | (0.49–0.79)
p-value | p<0.0001

Figure 7: Kaplan-Meier Curves for Overall Survival in PARAMOUNT

Treatment of Recurrent Disease After Prior Chemotherapy

The efficacy of pemetrexed was evaluated in Study JMEI (NCT00004881), a multicenter, randomized (1:1), open-label study conducted in patients with Stage III or IV NSCLC that had recurred or progressed following one prior chemotherapy regimen for advanced disease. Patients were randomized to receive pemetrexed 500 mg/m^2 intravenously or docetaxel 75 mg/m^2 as a 1-hour intravenous infusion once every 21 days. Patients randomized to pemetrexed also received folic acid and vitamin B12. The study was designed to show that overall survival with pemetrexed was non-inferior to docetaxel, as the major efficacy outcome measure, and that overall survival was superior for patients randomized to pemetrexed compared to docetaxel, as a secondary outcome measure.

A total of 571 patients were enrolled with 283 patients randomized to pemetrexed and 288 patients randomized to docetaxel. The median age was 58 years (range 22 to 87 years); 72% were male; 71% were White, 24% were Asian, 2.8% were Black or African American, 1.8% were Hispanic or Latino, and <2% were other ethnicities; 88% had an ECOG PS of 0 or 1. With regard to tumor characteristics, 75% had Stage IV disease; 53% had adenocarcinoma, 30% had squamous histology; 8% large cell; and 9% had other histologic subtypes of NSCLC.

The efficacy results in the overall population and in subgroup analyses based on histologic subtype are provided in Tables 13 and 14, respectively. Study JMEI did not show an improvement in overall survival in the intent-to-treat population. In subgroup analyses, there was no evidence of a treatment effect on survival in patients with squamous NSCLC; the absence of a treatment effect in patients with NSCLC of squamous histology was also observed in Studies JMDB and JMEN [see Clinical Studies (14.1)].

Table 13: Efficacy Results in Study JMEI
Efficacy Parameter | Pemetrexed (N=283) | Docetaxel (N=288)
Overall survival
Median (months) | 8.3 | 7.9
(95% CI) | (7.0–9.4) | (6.3–9.2)
Hazard ratio [Hazard ratios are not adjusted for multiplicity or for stratification variables.] | 0.99
(95% CI) | (0.82–1.20)
Progression-free survival
Median (months) | 2.9 | 2.9
(95% CI) | (2.4–3.1) | (2.7–3.4)
Hazard ratio | 0.97
(95% CI) | (0.82–1.16)
Overall response rate | 8.5% | 8.3%
(95% CI) | (5.2–11.7) | (5.1–11.5)

Table 14: Exploratory Efficacy Analyses by Histologic Subgroup in Study JMEI
Histologic Subgroups | Pemetrexed (N=283) | Docetaxel (N=288)
Non-squamous NSCLC (N=399)
Median (months) | 9.3 | 8.0
(95% CI) | (7.8–9.7) | (6.3–9.3)
HR [Hazard ratio unadjusted for multiple comparisons.] | 0.89
(95% CI) | (0.71–1.13)
Adenocarcinoma (N=301)
Median (months) | 9.0 | 9.2
(95% CI) | (7.6–9.6) | (7.5–11.3)
HR | 1.09
(95% CI) | (0.83–1.44)
Large Cell (N=47)
Median (months) | 12.8 | 4.5
(95% CI) | (5.8–14.0) | (2.3–9.1)
HR | 0.38
(95% CI) | (0.18–0.78)
Other [Primary diagnosis of NSCLC not specified as adenocarcinoma, large cell carcinoma, or squamous cell carcinoma.] (N=51)
Median (months) | 9.4 | 7.9
(95% CI) | (6.0–10.1) | (4.0–8.9)
HR | 0.62
(95% CI) | (0.32–1.23)
Squamous NSCLC (N=172)
Median (months) | 6.2 | 7.4
(95% CI) | (4.9–8.0) | (5.6–9.5)
HR | 1.32
(95% CI) | (0.93–1.86)

14.2 Mesothelioma

The efficacy of pemetrexed was evaluated in Study JMCH (NCT00005636), a multicenter, randomized (1:1), single-blind study conducted in patients with MPM who had received no prior chemotherapy. Patients were randomized (n=456) to receive pemetrexed 500 mg/m^2 intravenously over 10 minutes followed 30 minutes later by cisplatin 75 mg/m^2 intravenously over two hours on Day 1 of each 21-day cycle or to receive cisplatin 75 mg/m^2 intravenously over 2 hours on Day 1 of each 21-day cycle; treatment continued until disease progression or intolerable toxicity. The study was modified after randomization and treatment of 117 patients to require that all patients receive folic acid 350 mcg to 1000 mcg daily beginning 1 to 3 weeks prior to the first dose of pemetrexed and continuing until 1 to 3 weeks after the last dose, vitamin B12 1000 mcg intramuscularly 1 to 3 weeks prior to first dose of pemetrexed and every 9 weeks thereafter, and dexamethasone 4 mg orally, twice daily, for 3 days starting the day prior to each pemetrexed dose. Randomization was stratified by multiple baseline variables including KPS, histologic subtype (epithelial, mixed, sarcomatoid, other), and gender. The major efficacy outcome measure was overall survival and additional efficacy outcome measures were time to disease progression, overall response rate, and response duration.

A total of 448 patients received at least one dose of protocol-specified therapy; 226 patients were randomized to and received at least one dose of pemetrexed plus cisplatin, and 222 patients were randomized to and received cisplatin. Among the 226 patients who received cisplatin with pemetrexed, 74% received full supplementation with folic acid and vitamin B12 during study therapy, 14% were never supplemented, and 12% were partially supplemented. Across the study population, the median age was 61 years (range: 20 to 86 years); 81% were male; 92% were White, 5% were Hispanic or Latino, 3.1% were Asian, and <1% were other ethnicities; and 54% had a baseline KPS score of 90–100% and 46% had a KPS score of 70–80%. With regard to tumor characteristics, 46% had Stage IV disease, 31% Stage III, 15% Stage II, and 7% Stage I disease at baseline; the histologic subtype of mesothelioma was epithelial in 68% of patients, mixed in 16%, sarcomatoid in 10% and other histologic subtypes in 6%. The baseline demographics and tumor characteristics of the subgroup of fully supplemented patients was similar to the overall study population.

The efficacy results from Study JMCH are summarized in Table 15 and Figure 8.

Table 15: Efficacy Results in Study JMCH
Efficacy Parameter | All Randomized and Treated Patients (N=448) |  | Fully Supplemented Patients (N=331)
Efficacy Parameter | Pemetrexed/Cisplatin (N=226) | Cisplatin (N=222) | Pemetrexed/Cisplatin (N=168) | Cisplatin (N=163)
Median overall survival (months) | 12.1 | 9.3 | 13.3 | 10.0
(95% CI) | (10.0–14.4) | (7.8–10.7) | (11.4–14.9) | (8.4–11.9)
Hazard ratio [Hazard ratios are not adjusted for stratification variables.] | 0.77 |  | 0.75
Log rank p-value | 0.020 |  | NA [Not a pre-specified analysis.]

Figure 8: Kaplan-Meier Curves for Overall Survival in Study JMCH

Based upon prospectively defined criteria (modified Southwest Oncology Group methodology) the objective tumor response rate for pemetrexed plus cisplatin was greater than the objective tumor response rate for cisplatin alone. There was also improvement in lung function (forced vital capacity) in the pemetrexed plus cisplatin arm compared to the control arm.

15 REFERENCES

1. "OSHA Hazardous Drugs." OSHA. [https://www.osha.gov/hazardous-drugs]

16 HOW SUPPLIED/STORAGE AND HANDLING

How Supplied

Pemetrexed Injection is a clear, colorless to pale yellow ready-to-dilute solution in a single-dose vial for intravenous infusion.

NDC 0409-1045-01: Carton containing one (1) single-dose vial, 100 mg/4 mL (25 mg/mL).

NDC 0409-2188-01: Carton containing one (1) single-dose vial, 500 mg/20 mL (25 mg/mL).

NDC 0409-3532-01: Carton containing one (1) single-dose vial, 1 g/40 mL (25 mg/mL).

Storage and Handling

Store Pemetrexed Injection at controlled refrigerated temperature, 2°C to 8°C (36°F to 46°F).

Pemetrexed Injection is a hazardous drug. Follow applicable special handling and disposal procedures. [see References (15)]

17 PATIENT COUNSELING INFORMATION

Advise the patient to read the FDA-approved patient labeling (Patient Information).

Premedication and Concomitant Medication: Instruct patients to take folic acid as directed and to keep appointments for vitamin B12 injections to reduce the risk of treatment-related toxicity. Instruct patients of the requirement to take corticosteroids to reduce the risks of treatment-related toxicity [see Dosage and Administration (2.4) and Warnings and Precautions (5.1)].

Myelosuppression: Inform patients of the risk of low blood cell counts and instruct them to immediately contact their physician for signs of infection, fever, bleeding, or symptoms of anemia [see Warnings and Precautions (5.1)].

Renal Failure: Inform patients of the risks of renal failure, which may be exacerbated in patients with dehydration arising from severe vomiting or diarrhea. Instruct patients to immediately contact their healthcare provider for a decrease in urine output [see Warnings and Precautions (5.2)].

Bullous and Exfoliative Skin Disorders: Inform patients of the risks of severe and exfoliative skin disorders. Instruct patients to immediately contact their healthcare provider for development of bullous lesions or exfoliation in the skin or mucous membranes [see Warnings and Precautions (5.3)].

Interstitial Pneumonitis: Inform patients of the risks of pneumonitis. Instruct patients to immediately contact their healthcare provider for development of dyspnea or persistent cough [see Warnings and Precautions (5.4)].

Radiation Recall: Inform patients who have received prior radiation of the risks of radiation recall. Instruct patients to immediately contact their healthcare provider for development of inflammation or blisters in an area that was previously irradiated [see Warnings and Precautions (5.5)].

Increased Risk of Toxicity with Ibuprofen in Patients with Renal Impairment: Advise patients with mild to moderate renal impairment of the risks associated with concomitant ibuprofen use and instruct them to avoid use of all ibuprofen containing products for 2 days before, the day of, and 2 days following administration of Pemetrexed Injection [see Dosage and Administration (2.5), Warnings and Precautions (5.6), and Drug Interactions (7)].

Embryo-Fetal Toxicity: Advise females of reproductive potential and males with female partners of reproductive potential of the potential risk to a fetus [see Warnings and Precautions (5.7) and Use in Specific Populations (8.1)]. Advise females of reproductive potential to use effective contraception during treatment with Pemetrexed Injection and for 6 months after the last dose. Advise females to inform their prescriber of a known or suspected pregnancy. Advise males with female partners of reproductive potential to use effective contraception during treatment with Pemetrexed Injection and for 3 months after the last dose [see Warnings and Precautions (5.7) and Use in Specific Populations (8.3)].

Lactation: Advise women not to breastfeed during treatment with Pemetrexed Injection and for 1 week after the last dose [see Use in Specific Populations (8.2)].

This product's label may have been updated. For current full prescribing information, please visit www.pfizer.com.

Manufactured by: Zydus Hospira Oncology Private Ltd.
Ahmedabad 382-213, Gujarat, India.

Distributed by: Hospira, Inc., Lake Forest, IL 60045 USA

LAB-1430-1.0

PATIENT INFORMATION
Pemetrexed (peh-meh-TREX-ed) Injection
for intravenous use

What is Pemetrexed Injection?

Pemetrexed Injection is a prescription medicine used to treat:

- a kind of lung cancer called non-squamous non-small cell lung cancer (NSCLC). Pemetrexed Injection is used:
  - as the first treatment in combination with cisplatin when your lung cancer has spread (advanced NSCLC).
  - alone as maintenance treatment after you have received 4 cycles of chemotherapy that contains platinum for first treatment of your advanced NSCLC and your cancer has not progressed.
  - alone when your lung cancer has returned or spread after prior chemotherapy.
Pemetrexed Injection is not for use for the treatment of people with squamous cell, non-small cell lung cancer.
- a kind of cancer called malignant pleural mesothelioma. This cancer affects the lining of the lungs and chest wall. Pemetrexed Injection is used in combination with cisplatin as the first treatment for malignant pleural mesothelioma that cannot be removed by surgery or you are not able to have surgery.

Pemetrexed Injection has not been shown to be safe and effective in children.

Do not take Pemetrexed Injection if you have had a severe allergic reaction to any medicine that contains pemetrexed.

Before taking Pemetrexed Injection, tell your healthcare provider about all of your medical conditions, including if you:

- have kidney problems.
- have had radiation therapy.
- are pregnant or plan to become pregnant. Pemetrexed Injection can harm your unborn baby.
  Females who are able to become pregnant:
  Your healthcare provider will check to see if you are pregnant before you start treatment with Pemetrexed Injection.
  You should use effective birth control (contraception) during treatment with Pemetrexed Injection and for 6 months after the last dose. Tell your healthcare provider right away if you become pregnant or think you are pregnant during treatment with Pemetrexed Injection.
  Males with female partners who are able to become pregnant should use effective birth control (contraception) during treatment with Pemetrexed Injection and for 3 months after the last dose.
- are breastfeeding or plan to breastfeed. It is not known if Pemetrexed Injection passes into breast milk. Do not breastfeed during treatment with Pemetrexed Injection and for 1 week after the last dose.

Tell your healthcare provider about all the medicines you take, including prescription and over-the-counter medicines, vitamins, and herbal supplements.
Tell your healthcare provider if you have kidney problems and take a medicine that contains ibuprofen. You should avoid taking ibuprofen for 2 days before, the day of, and 2 days after receiving treatment with Pemetrexed Injection.

How is Pemetrexed Injection given?

- It is very important to take folic acid and vitamin B12 during your treatment with Pemetrexed Injection to lower your risk of harmful side effects.
  - Take folic acid exactly as prescribed by your healthcare provider 1 time a day, beginning 7 days (1 week) before your first dose of Pemetrexed Injection and continue taking folic acid until 21 days (3 weeks) after your last dose of Pemetrexed Injection.
  - Your healthcare provider will give you vitamin B12 injections during treatment with Pemetrexed Injection. You will get your first vitamin B12 injection 7 days (1 week) before your first dose of Pemetrexed Injection, and then every 3 cycles.
- Your healthcare provider will prescribe a medicine called corticosteroid for you to take 2 times a day for 3 days, beginning the day before each treatment with Pemetrexed Injection.
- Pemetrexed Injection is given to you by intravenous (IV) infusion into your vein. The infusion is given over 10 minutes.
- Pemetrexed Injection is usually given once every 21 days (3 weeks).

What are the possible side effects of Pemetrexed Injection?

Pemetrexed Injection can cause serious side effects, including:

- Low blood cell counts. Low blood cell counts can be severe, including low white blood cell counts (neutropenia), low platelet counts (thrombocytopenia), and low red blood cell counts (anemia). Your healthcare provider will do blood tests to check your blood cell counts regularly during your treatment with Pemetrexed Injection. Tell your healthcare provider right away if you have any signs of infection, fever, bleeding, or severe tiredness during your treatment with Pemetrexed Injection.
- Kidney problems, including kidney failure. Pemetrexed Injection can cause severe kidney problems that can lead to death. Severe vomiting or diarrhea can lead to loss of fluids (dehydration) which may cause kidney problems to become worse. Tell your healthcare provider right away if you have a decrease in the amount of urine you make.
- Severe skin reactions. Severe skin reactions that may lead to death can happen with Pemetrexed Injection. Tell your healthcare provider right away if you develop blisters, skin sores, skin peeling, or painful sores, or ulcers in your mouth, nose, throat or genital area.
- Lung problems (pneumonitis). Pemetrexed Injection can cause serious lung problems that can lead to death. Tell your healthcare provider right away if you get any new or worsening symptoms of shortness of breath, cough, or fever.
- Radiation recall. Radiation recall is a skin reaction that can happen in people who have received radiation treatment in the past and are treated with Pemetrexed Injection. Tell your healthcare provider if you get swelling, blistering, or a rash that looks like a sunburn in an area that was previously treated with radiation.

The most common side effects of Pemetrexed Injection when given alone are:

- tiredness

- nausea

- loss of appetite

The most common side effects of Pemetrexed Injection when given with cisplatin are:

- vomiting
- swelling or sores in your mouth or sore throat
- constipation

- low white blood cell counts (neutropenia)
- low platelet counts (thrombocytopenia)
- low red blood cell counts (anemia)

Pemetrexed Injection may cause fertility problems in males. This may affect your ability to father a child. It is not known if these effects are reversible. Talk to your healthcare provider if this is a concern for you.
Your healthcare provider will do blood tests to check for side effects during treatment with Pemetrexed Injection. Your healthcare provider may change your dose of Pemetrexed Injection, delay treatment, or stop treatment if you have certain side effects.
Tell your healthcare provider if you have any side effect that bothers you or that does not go away.
These are not all of the possible side effects of Pemetrexed Injection. For more information, ask your healthcare provider or pharmacist.
Call your doctor for medical advice about side effects. You may report side effects to FDA at 1-800-FDA-1088.

General information about the safe and effective use of Pemetrexed Injection.
Medicines are sometimes prescribed for purposes other than those listed in a Patient Information leaflet.
You can ask your pharmacist or healthcare provider for information about Pemetrexed Injection that is written for health professionals.

What are the ingredients in Pemetrexed Injection?
Active ingredient: pemetrexed
Inactive ingredient: monothioglycerol, water for injection and may contain sodium hydroxide for pH adjustment.
Manufactured by: Zydus Hospira Oncology Private Ltd.
Ahmedabad 382-213, Gujarat, India.

Distributed by: Hospira, Inc., Lake Forest, IL 60045 USA
LAB-1432-1.0
For more information, please visit http://www.pfizer.com.

This Patient Information has been approved by the U.S. Food and Drug Administration. Issued: 6/2022

PRINCIPAL DISPLAY PANEL - 4 mL Vial Label

Rx only
NDC 0409-1045-01

Single Dose Vial - Discard Unused Portion
Sterile

Pemetrexed Injection
100 mg/4 mL
(25 mg/mL)

For Intravenous Infusion After Dilution
Warning: Hazardous Drug

Store refrigerated at 2°C to 8°C (36°F to 46°F).

PRINCIPAL DISPLAY PANEL - 4 mL Vial Carton

1 x 4 mL vial
NDC 0409-1045-01

Sterile
Rx only

Pemetrexed
Injection
100 mg/4 mL
(25 mg/mL)

For Intravenous
Infusion After Dilution

Single Dose Vial
Discard Unused Portion

Hospira

Warning: Hazardous Drug

PRINCIPAL DISPLAY PANEL - 20 mL Vial Label

Rx only
NDC 0409-2188-01

Single Dose Vial - Discard Unused Portion
Sterile

Pemetrexed Injection
500 mg/20 mL
(25 mg/mL)

For Intravenous Infusion After Dilution

Store refrigerated at 2°C to 8°C (36°F to 46°F).

Warning:
Hazardous Drug

PRINCIPAL DISPLAY PANEL - 20 mL Vial Carton

1 x 20 mL vial
NDC 0409-2188-01

Sterile
Rx only

Pemetrexed
Injection
500 mg/20 mL
(25 mg/mL)

For Intravenous
Infusion After Dilution

Single Dose Vial
Discard Unused Portion

Hospira

Warning: Hazardous Drug

PRINCIPAL DISPLAY PANEL - 40 mL Vial Label

Rx only
NDC 0409-3532-01

Single Dose Vial - Discard Unused Portion
Sterile

Pemetrexed Injection
1 g/40 mL
(25 mg/mL)

For Intravenous Infusion After Dilution

Store refrigerated at 2°C to 8°C (36°F to 46°F).

Hospira

Warning: Hazardous Drug

PRINCIPAL DISPLAY PANEL - 40 mL Vial Carton

1 x 40 mL vial
NDC 0409-3532-01

Sterile
Rx only

Pemetrexed
Injection
1 g/40 mL
(25 mg/mL)

For Intravenous
Infusion After Dilution

Single Dose Vial
Discard Unused Portion

Hospira

Warning: Hazardous Drug